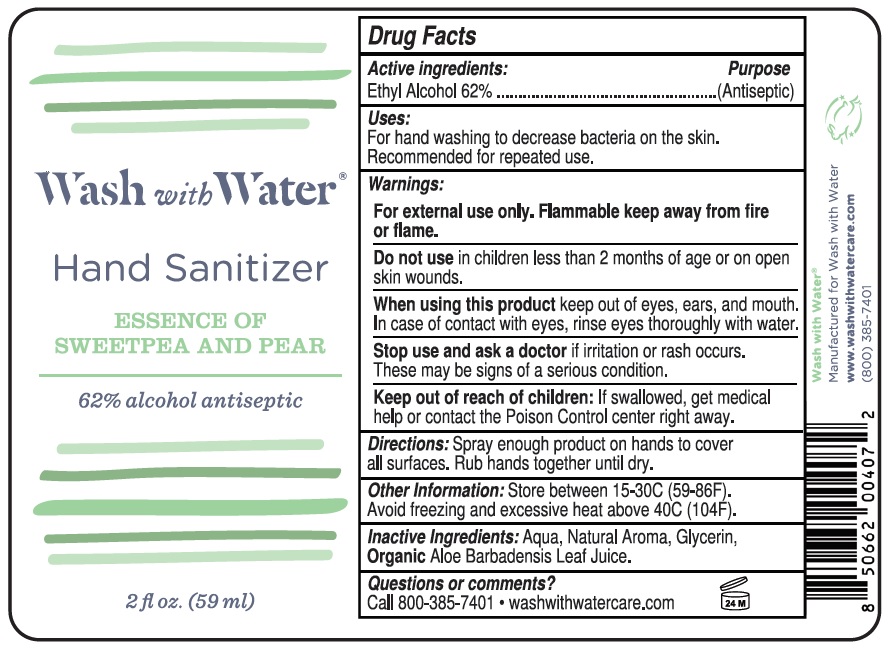 DRUG LABEL: Wash with Water Hand Sanitizer
NDC: 81449-062 | Form: SPRAY
Manufacturer: Wash With Water
Category: otc | Type: HUMAN OTC DRUG LABEL
Date: 20210202

ACTIVE INGREDIENTS: ALCOHOL 62 mL/100 mL
INACTIVE INGREDIENTS: WATER; GLYCERIN; ALOE VERA LEAF

Wash with Water® Hand Sanitizer

Active ingredients:

Ethyl Alcohol 62%

Purpose

(Antiseptic)

Uses:

For hand washing to decrease bacteria on the skin. Recommended for repeated use.

Warnings:

For external use only. Flammable keep away from fire or flame.

Do not use in children less than 2 months of age or on open skin wounds.

When using this product keep out of eyes, ears, and mouth. In case of contact with eyes, rinse eyes thoroughly with water.

Stop use and ask a doctor if irritation or rash occurs. These may be signs of a serious condition.

Keep out of reach of children: If swallowed, get medical help or contact the Poison Control center right away.

Directions:

Spray enough product on hands to cover all surfaces. Rub hands together until dry.

Other Information:

Store between 15-30C (59-86F). Avoid freezing and excessive heat above 40C (104F).

Inactive Ingredients:

Aqua, Natural Aroma, Glycerin, Organic Aloe Barbadensis Leaf Juice.

Questions or comments?

Call 800-385-7401 • washwithwatercare.com

ESSENCE OF SWEETPEA AND PEAR

62% alcohol antiseptic

Wash with Water®

Manufactured for Wash with Water

www.washwithwatercare.com

(800) 385-7401